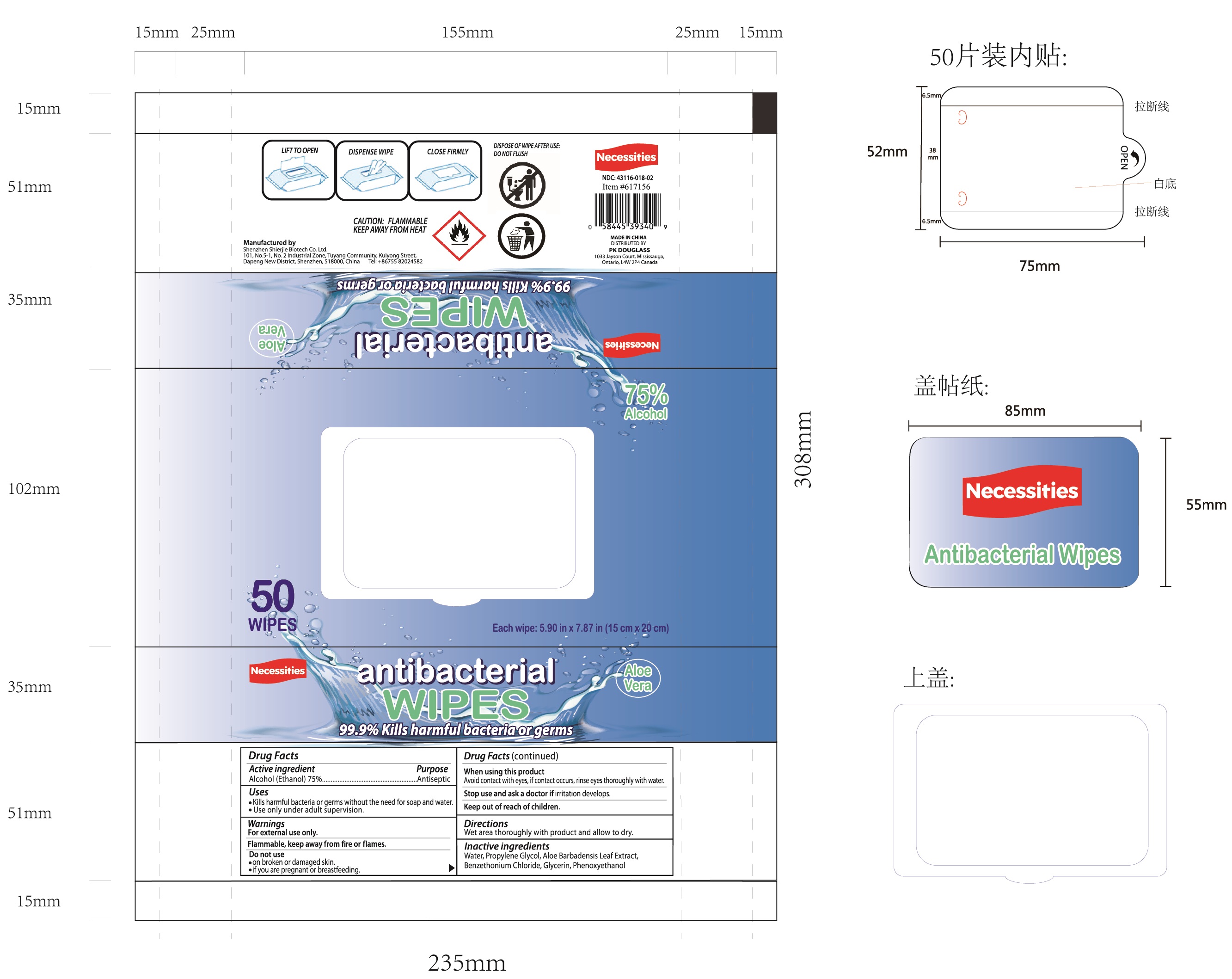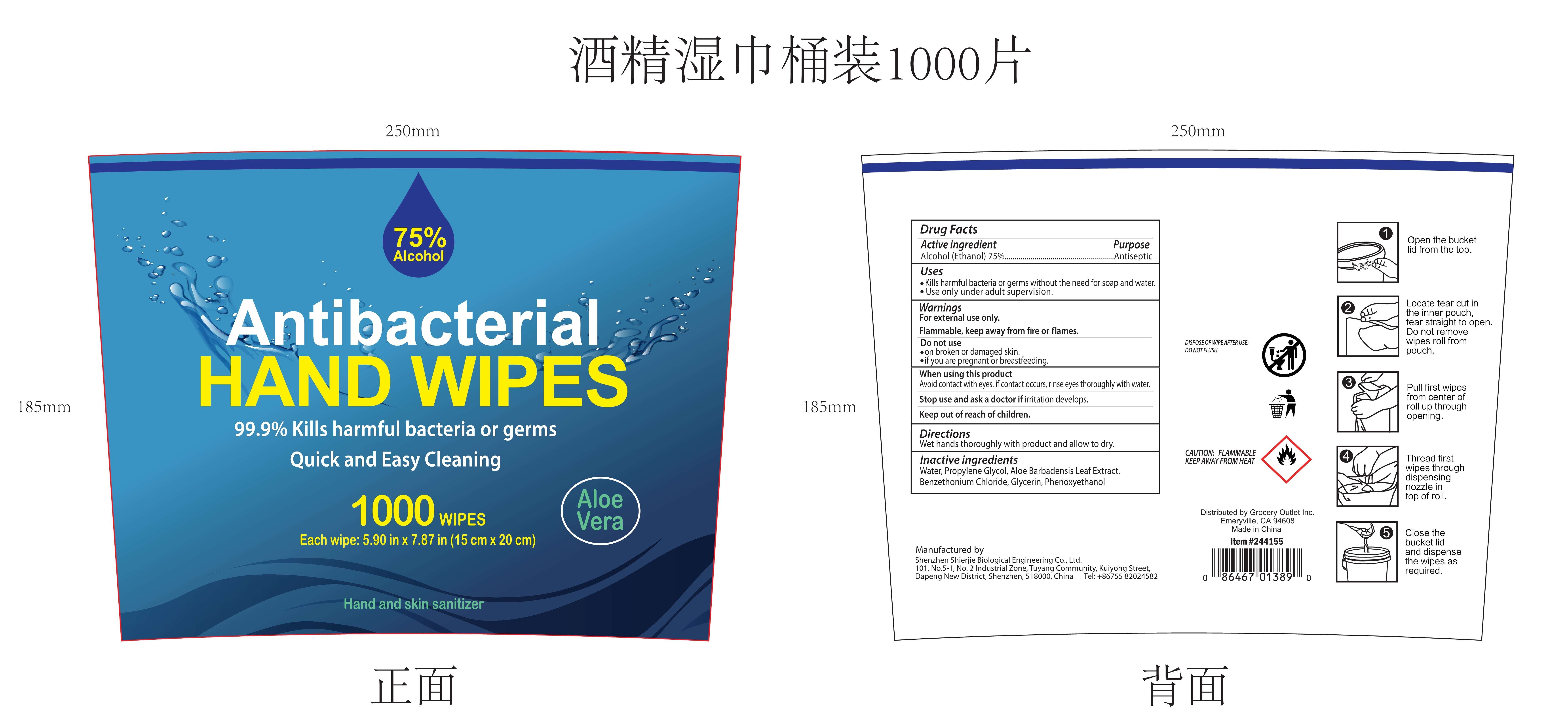 DRUG LABEL: antibacterial WIPES
NDC: 43116-021 | Form: CLOTH
Manufacturer: Shenzhen Shierjie Biological Engineering Co., LTD
Category: otc | Type: HUMAN OTC DRUG LABEL
Date: 20201122

ACTIVE INGREDIENTS: ALCOHOL 75 mL/100 1
INACTIVE INGREDIENTS: PHENOXYETHANOL; PROPYLENE GLYCOL; BENZETHONIUM CHLORIDE; ALOE VERA LEAF; GLYCERIN; WATER

43116-021
antibacterial WIPES

Active Ingredient

Alcohol (Ethanol)75%

Purpose

Antiseptic

Uses

Kills harmful bacteria or germs without the need for soap and water
Use only under adult supervision

Warnings

For external use only
Flammable, keep away from fire or flames.

DO NOT USE

on broken or damaged skin.
if you are pregnant or breastfeeding

WHEN USING

Avoid contact with eyes, if contact occurs, rinse eyes thoroughly with water.

Stop use and ask a doctor if irritation develops

Keep out of reach of children

Directions

Wet area thoroughly with product and allow to dry

Other information

/

Inactive ingredients

water, Propylene glycol, Aloe Barbadensis Leaf Extract, Benzethonium Chloride, Glycerin, Phenoxyethanol